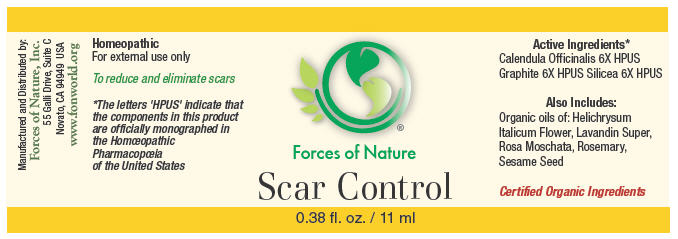 DRUG LABEL: Scar Control
NDC: 51393-7111 | Form: SOLUTION/ DROPS
Manufacturer: Forces of Nature
Category: homeopathic | Type: HUMAN OTC DRUG LABEL
Date: 20100824

ACTIVE INGREDIENTS: CALENDULA OFFICINALIS FLOWERING TOP 6 [hp_X]/1000 mL; Graphite 6 [hp_X]/1000 mL; Silicon Dioxide 6 [hp_X]/1000 mL
INACTIVE INGREDIENTS: HELICHRYSUM ITALICUM FLOWERING TOP

Scar Control

Drug Facts

Indications

To reduce and eliminate scars

ACTIVE INGREDIENT

PURPOSE

Homeopathic Active Ingredients [The letters 'HPUS' indicate that the components in this product are officially monographed in the Homœopathic Pharmacopœia of the United States.]
Calendula Officinalis 6X HPUS | Promotes healthy skin and healing
Geranium Maculatum 6X HPUS | Heals ulcers in skin
Silicea 6X HPUS | Remedy for painful scars, keloids, old scars become painful

Also Contains

Helichrysum Italicum Flower Oil, Certified organic Lavandin Super Oil, Rosa Moschata Oil, Rosemary Oil, Certified organic Sesame Seed Oil

Directions

Simply rub one to three drops into area of treatment. Apply three times per day.

Warnings

If skin symptoms worsen consult a health care professional. Some individuals may be sensitive to tea tree or other oils. Begin with a small drop to determine if the product causes any increased redness or irritation and discontinue use if it irritates your skin.

PREGNANCY OR BREAST FEEDING

As with all medication, if you are pregnant or breast-feeding, ask a health professional before use.

Keep out of the reach of children.

WHEN USING

For external use only. If accidental ingestion of more than a few drops, or an adverse reaction occurs, seek medical help. Do not apply to the eyes. Keep all medicines out of the reach of children. Stop use and ask a doctor if condition worsens.

Manufactured by:
Forces of Nature, Inc.
55 Galli Drive, Suite C
Novato, CA 94949 USA
www.fonworld.org

Product questions?

877-975-3797

NDC#: 51393-7111-1 (11ml) // 51393-7111-2 (33ml)

Principal Display Panel - 11 ml Bottle Label

Forces of Nature

Scar Control

0.38 fl. oz. / 11 ml